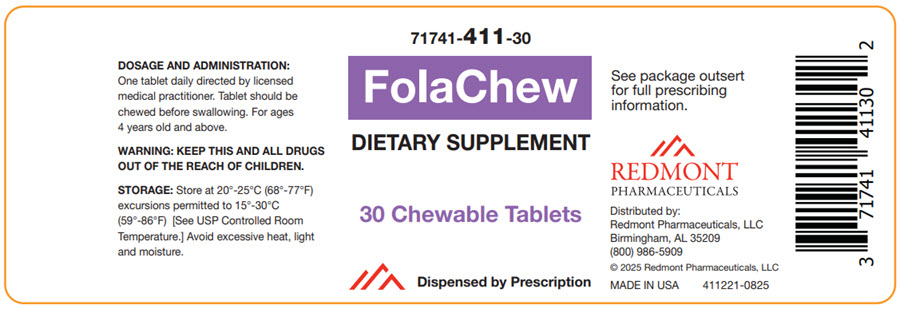 DRUG LABEL: FolaChew
NDC: 71741-411 | Form: TABLET
Manufacturer: Redmont Pharmaceuticals, LLC
Category: other | Type: DIETARY SUPPLEMENT
Date: 20250829

ACTIVE INGREDIENTS: BETA CAROTENE 900 ug/1 1; Ascorbic Acid 60 mg/1 1; Sodium Ascorbate 30 mg/1 1; Cholecalciferol 20 ug/1 1; .ALPHA.-TOCOPHEROL ACETATE 15 mg/1 1; THIAMINE MONONITRATE 1.2 mg/1 1; Riboflavin 1.3 mg/1 1; NIACIN 16 mg/1 1; PYRIDOXINE HYDROCHLORIDE 1.7 mg/1 1; Folic Acid 0.400 mg/1 1; 5-METHYLTETRAHYDROFOLIC ACID 0.600 mg/1 1; Cyanocobalamin 0.0024 mg/1 1
INACTIVE INGREDIENTS: Sorbitol; HYPROMELLOSE, UNSPECIFIED; Locust Bean Gum; Carrageenan; MAGNESIUM PALMITOSTEARATE; Stearic Acid

FolaChew

HEALTH CLAIM

71741-411-30
Multivitamin Chewable Tablet

DESCRIPTION

FolaChew is a chewable prescription multivitamin.

ACTIVE INGREDIENTS

Supplement Facts
Serving size: 1 Tablet
Amount per Serving: | %Daily Value
Vitamin A (as Beta-Carotene) | 900 mcg RAE | 100%
Vitamin C (as Sodium Ascorbate and Ascorbic Acid) | 90 mg | 100%
Vitamin D3 (as Cholecalciferol) | 20 mcg | 100%
Vitamin E (as dl-Alpha Tocopherol Acetate) | 15 mg | 100%
Thiamin (Vitamin B-1 as Thiamine Mononitrate) | 1.2 mg | 100%
Riboflavin (Vitamin B-2) | 1.3 mg | 100%
Niacin (as Niacinamide) | 16 mg | 100%
Vitamin B6 (as Pyridoxine HCl) | 1.7 mg | 100%
Folate | 1.67 mg DFE | 418%
(from Folic Acid) | 0.67 mg DFE
(as 5-Methyl Tetrahydrofolate, Calcium Salt) | 1 mg DFE
Vitamin B12 (as Cyanocobalamin) | 2.4 mcg | 100%

OTHER INGREDIENTS

Sorbitol, Natural and Artificial Flavors, Contains Less Than 2% of: Hydroxypropyl Methylcellulose, Locust Bean Gum, Carrageenan, Magnesium Stearate, Stearic Acid.

Preservative Free and Gluten Free. No Starch, Artificial Colors, Wheat, Yeast or Corn Added.

INDICATIONS AND USAGE

FolaChew is indicated to provide significant amounts of Vitamins A, C, D, E, thiamine, riboflavin, niacin, vitamin B6, vitamin B12, and folate to supplement the diet, and to help assure that nutritional deficiencies of these vitamins will not develop. FolaChew is formulated to provide essential nutrients, tailored to the needs of all individuals ages 4 years old and above, promoting overall health, energy, and vitality.

CONTRAINDICATIONS

This product is contraindicated in patients with known hypersensitivity to any of its ingredients.

SAFE HANDLING WARNING

KEEP THIS AND ALL DRUGS OUT OF THE REACH OF CHILDREN.

PRECAUTIONS

Folic acid alone is improper therapy in the treatment of pernicious anemia and other megaloblastic anemias where vitamin B12 is deficient. Folic acid may obscure pernicious anemia in that hematologic remission can occur while neurological manifestations progress. FolaChew should only be used under the direction and supervision of a licensed medical practitioner.

ADVERSE REACTIONS

Allergic sensitization has been reported following both oral and parenteral administration of folic acid. You may report side effects by calling Redmont Pharmaceuticals, LLC at 1-800- 986-5909.

DOSAGE AND ADMINISTRATION

One tablet daily directed by licensed medical practitioner. Tablet should be chewed before swallowing.

HOW SUPPLIED

Bottle of 30 chewable tablets. Tablet is off-white, grape flavored, unscored, round.

*Redmont Pharmaceuticals does not represent this product code to be National Drug Code (NDC). The product code has been formatted to comply with standard industry practice for pharmacy and insurance computer systems.

STORAGE

Store at 20° to 25°C (68° to 77°F); excursions permitted to 15° to 30°C (59° to 86°F). [See USP Controlled Room Temperature.] Avoid excessive heat, light and moisture.

TAMPER EVIDIENT: Do not use if seal if broken or missing.

HEALTH CLAIM

MADE IN THE USA

Distributed by:
Redmont Pharmaceuticals, LLC
Birmingham, AL 35209
800-986-5909

These statements have not been evaluated by the Food and Drug Administration. This product is not intended to diagnose, treat, cure, or prevent any disease.

© 2025 Redmont Pharmaceuticals, LLC
411111-0825

PRINCIPAL DISPLAY PANEL - 30 Tablet Bottle Label

71741-411-30

FolaChew

DIETARY SUPPLEMENT

30 Chewable Tablets

Dispensed by Prescription